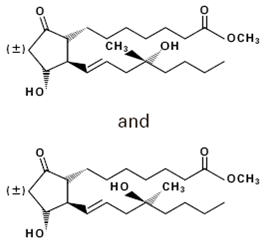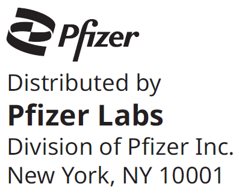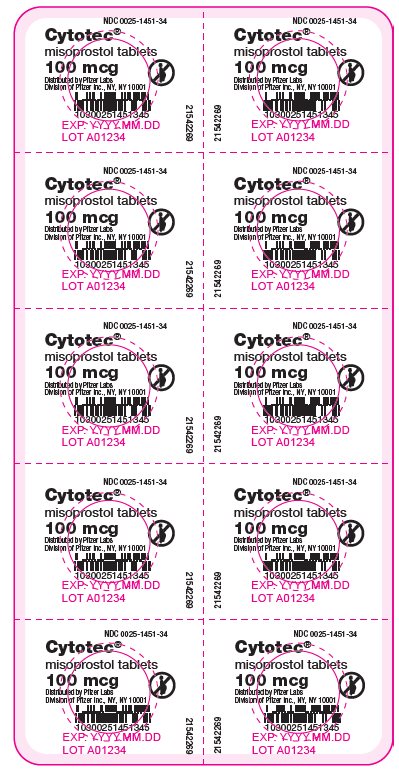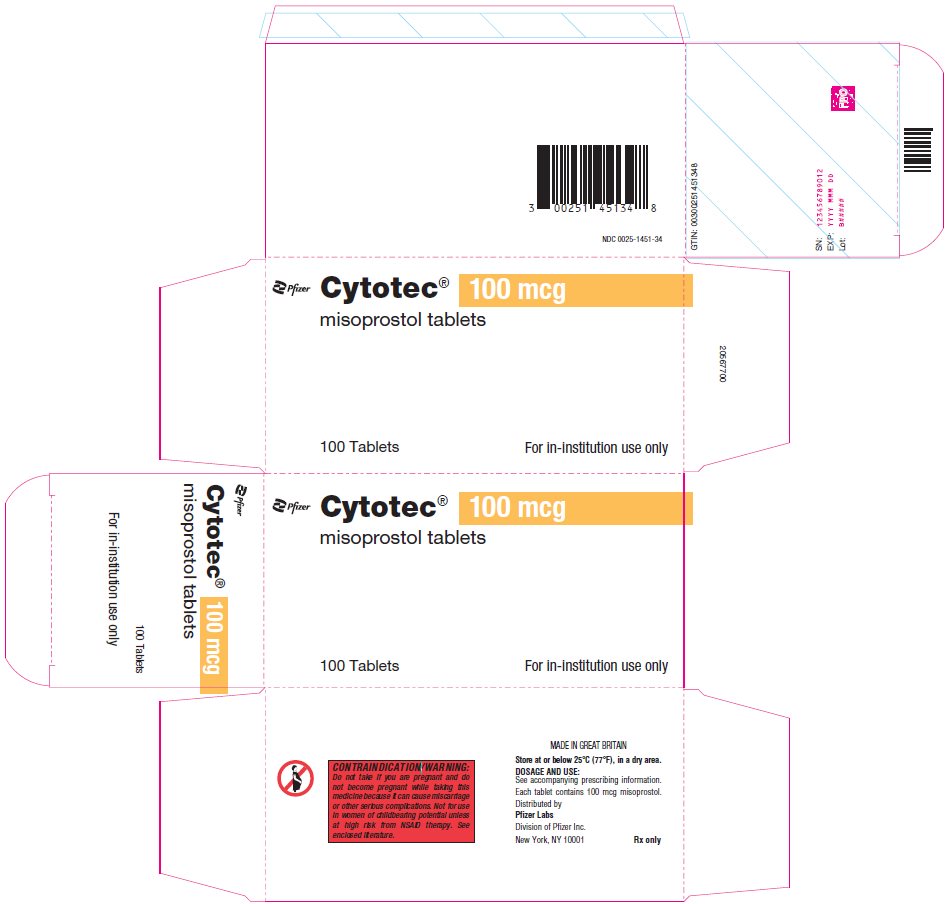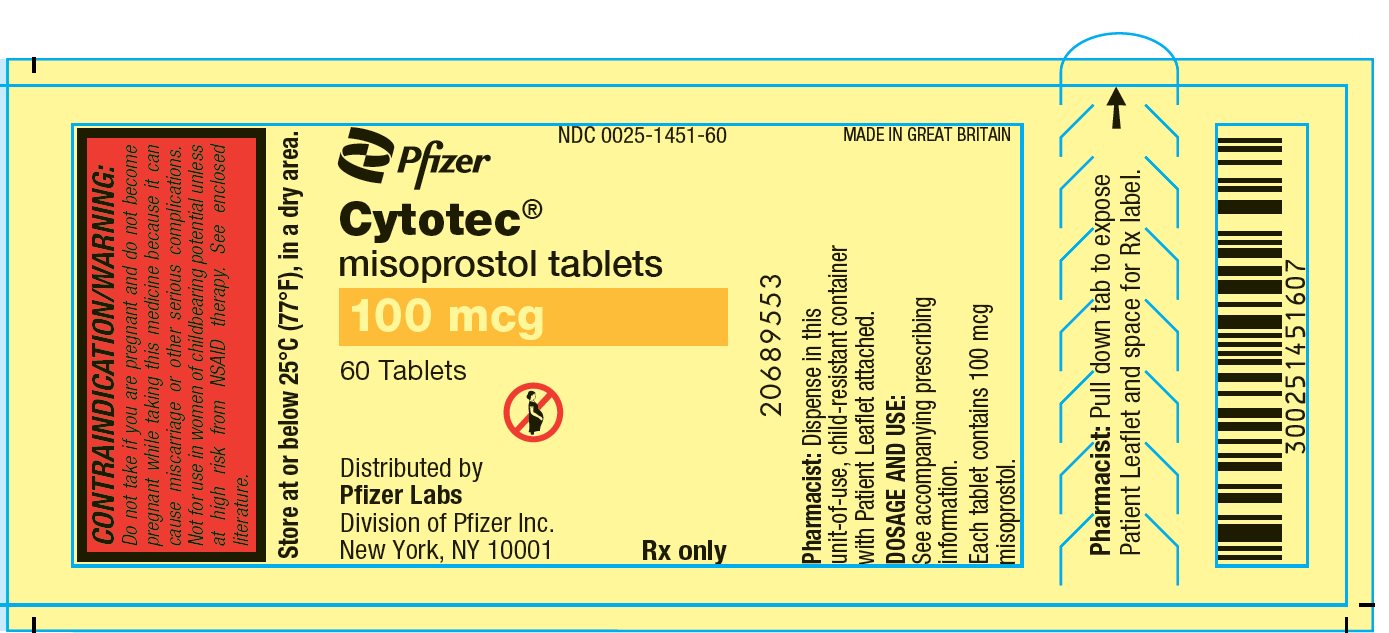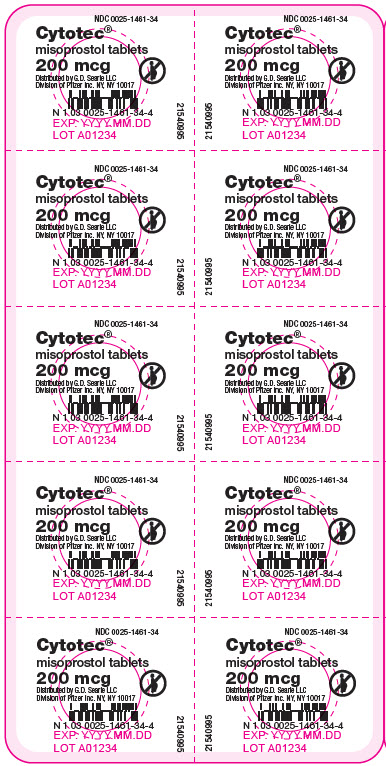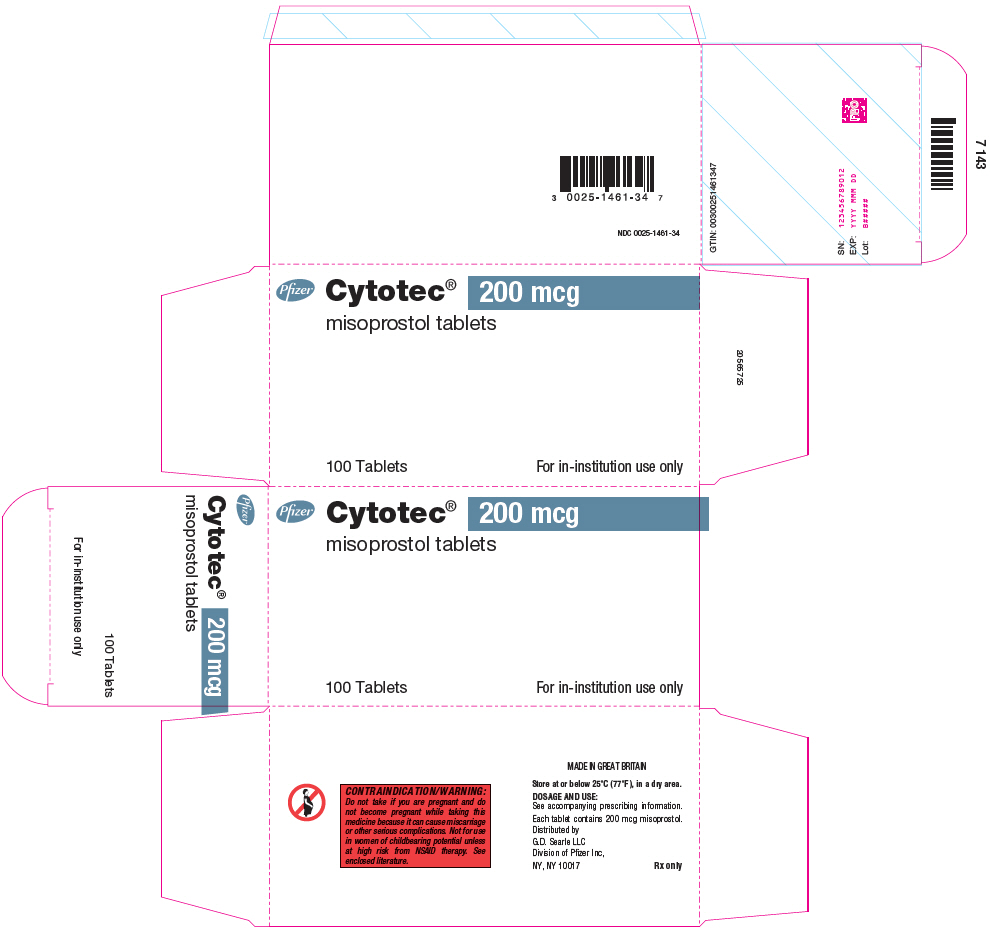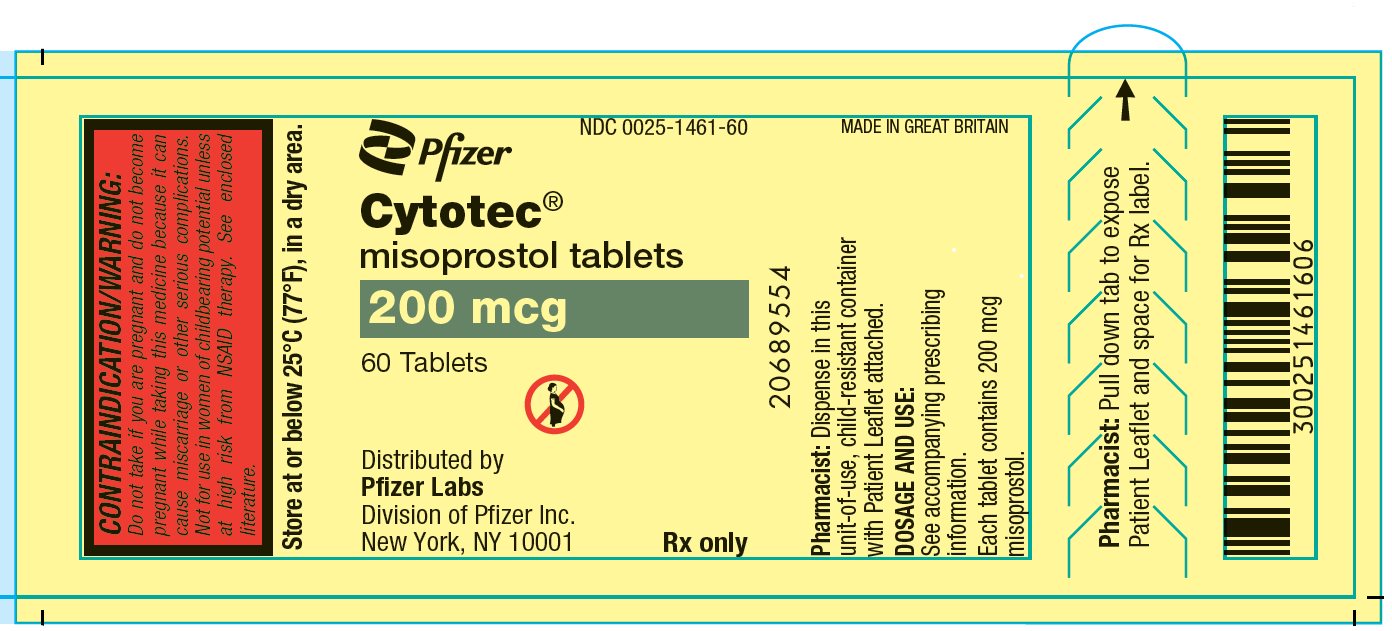 DRUG LABEL: Cytotec
NDC: 0025-1451 | Form: TABLET
Manufacturer: Pfizer Laboratories Div Pfizer Inc
Category: prescription | Type: HUMAN PRESCRIPTION DRUG LABEL
Date: 20250722

ACTIVE INGREDIENTS: MISOPROSTOL 100 ug/1 1
INACTIVE INGREDIENTS: HYDROGENATED CASTOR OIL; HYPROMELLOSE, UNSPECIFIED; MICROCRYSTALLINE CELLULOSE

Cytotec®
misoprostol tablets

WARNINGS

CYTOTEC (MISOPROSTOL) ADMINISTRATION TO WOMEN WHO ARE PREGNANT CAN CAUSE BIRTH DEFECTS, ABORTION, PREMATURE BIRTH OR UTERINE RUPTURE.

UTERINE RUPTURE HAS BEEN REPORTED WHEN CYTOTEC WAS ADMINISTERED IN PREGNANT WOMEN TO INDUCE LABOR OR TO INDUCE ABORTION. THE RISK OF UTERINE RUPTURE INCREASES WITH ADVANCING GESTATIONAL AGES AND WITH PRIOR UTERINE SURGERY, INCLUDING CESAREAN DELIVERY (see also PRECAUTIONS and LABOR AND DELIVERY).

CYTOTEC SHOULD NOT BE TAKEN BY PREGNANT WOMEN TO REDUCE THE RISK OF ULCERS INDUCED BY NONSTEROIDAL ANTI-INFLAMMATORY DRUGS (NSAIDs) (see CONTRAINDICATIONS, WARNINGS, and PRECAUTIONS).

PATIENTS MUST BE ADVISED OF THE ABORTIFACIENT PROPERTY AND WARNED NOT TO GIVE THE DRUG TO OTHERS.

Cytotec should not be used for reducing the risk of NSAID-induced ulcers in women of childbearing potential unless the patient is at high risk of complications from gastric ulcers associated with use of the NSAID, or is at high risk of developing gastric ulceration. In such patients, Cytotec may be prescribed if the patient

- has had a negative serum pregnancy test within 2 weeks prior to beginning therapy.
- is capable of complying with effective contraceptive measures.
- has received both oral and written warnings of the hazards of misoprostol, the risk of possible contraception failure, and the danger to other women of childbearing potential should the drug be taken by mistake.
- will begin Cytotec only on the second or third day of the next normal menstrual period.

DESCRIPTION

Cytotec oral tablets contain either 100 mcg or 200 mcg of misoprostol, a synthetic prostaglandin E1 analog.

Misoprostol contains approximately equal amounts of the two diastereomers presented below with their enantiomers indicated by (±):

C22H38O5 M.W. = 382.5

(±) methyl 11α, 16-dihydroxy-16-methyl-9-oxoprost-13E-en-1-oate

Misoprostol is a water-soluble, viscous liquid.

Inactive ingredients of tablets are hydrogenated castor oil, hypromellose, microcrystalline cellulose, and sodium starch glycolate.

CLINICAL PHARMACOLOGY

Pharmacokinetics

Misoprostol is extensively absorbed, and undergoes rapid de-esterification to its free acid, which is responsible for its clinical activity and, unlike the parent compound, is detectable in plasma. The alpha side chain undergoes beta oxidation and the beta side chain undergoes omega oxidation followed by reduction of the ketone to give prostaglandin F analogs.

In normal volunteers, Cytotec (misoprostol) is rapidly absorbed after oral administration with a Tmax of misoprostol acid of 12 ± 3 minutes and a terminal half-life of 20–40 minutes.

There is high variability of plasma levels of misoprostol acid between and within studies but mean values after single doses show a linear relationship with dose over the range of 200–400 mcg. No accumulation of misoprostol acid was noted in multiple dose studies; plasma steady state was achieved within two days.

Maximum plasma concentrations of misoprostol acid are diminished when the dose is taken with food and total availability of misoprostol acid is reduced by use of concomitant antacid. Clinical trials were conducted with concomitant antacid, however, so this effect does not appear to be clinically important.

Mean ± SD | Cmax(pg/ml) | AUC(0–4) (pg∙hr/ml) | Tmax(min)
Fasting | 811 ± 317 | 417 ± 135 | 14 ± 8
With Antacid | 689 ± 315 | 349 ± 108 [Comparisons with fasting results statistically significant, p<0.05.] | 20 ± 14
With High Fat Breakfast | 303 ± 176 | 373 ± 111 | 64 ± 79

After oral administration of radiolabeled misoprostol, about 80% of detected radioactivity appears in urine. Pharmacokinetic studies in patients with varying degrees of renal impairment showed an approximate doubling of T1/2, Cmax, and AUC compared to normals, but no clear correlation between the degree of impairment and AUC. In subjects over 64 years of age, the AUC for misoprostol acid is increased. No routine dosage adjustment is recommended in older patients or patients with renal impairment, but dosage may need to be reduced if the usual dose is not tolerated.

Drug interaction studies between misoprostol and several nonsteroidal anti-inflammatory drugs showed no effect on the kinetics of ibuprofen or diclofenac, and a 20% decrease in aspirin AUC, not thought to be clinically significant.

Pharmacokinetic studies also showed a lack of drug interaction with antipyrine and propranolol when these drugs were given with misoprostol. Misoprostol given for 1 week had no effect on the steady state pharmacokinetics of diazepam when the two drugs were administered 2 hours apart.

The serum protein binding of misoprostol acid is less than 90% and is concentration-independent in the therapeutic range.

After a single oral dose of misoprostol to nursing mothers, misoprostol acid was excreted in breast milk. The maximum concentration of misoprostol acid in expressed breast milk was achieved within 1 hour after dosing and was 7.6 pg/ml (CV 37%) and 20.9 pg/ml (CV 62%) after single 200 µg and 600 µg misoprostol administration, respectively. The misoprostol acid concentrations in breast milk declined to < 1 pg/ml at 5 hours post-dose.

Pharmacodynamics

Misoprostol has both antisecretory (inhibiting gastric acid secretion) and (in animals) mucosal protective properties. NSAIDs inhibit prostaglandin synthesis, and a deficiency of prostaglandins within the gastric mucosa may lead to diminishing bicarbonate and mucus secretion and may contribute to the mucosal damage caused by these agents. Misoprostol can increase bicarbonate and mucus production, but in man this has been shown at doses 200 mcg and above that are also antisecretory. It is therefore not possible to tell whether the ability of misoprostol to reduce the risk of gastric ulcer is the result of its antisecretory effect, its mucosal protective effect, or both.

In vitro studies on canine parietal cells using tritiated misoprostol acid as the ligand have led to the identification and characterization of specific prostaglandin receptors. Receptor binding is saturable, reversible, and stereospecific. The sites have a high affinity for misoprostol, for its acid metabolite, and for other E type prostaglandins, but not for F or I prostaglandins and other unrelated compounds, such as histamine or cimetidine. Receptor-site affinity for misoprostol correlates well with an indirect index of antisecretory activity. It is likely that these specific receptors allow misoprostol taken with food to be effective topically, despite the lower serum concentrations attained.

Misoprostol produces a moderate decrease in pepsin concentration during basal conditions, but not during histamine stimulation. It has no significant effect on fasting or postprandial gastrin nor on intrinsic factor output.

Effects on gastric acid secretion

Misoprostol, over the range of 50–200 mcg, inhibits basal and nocturnal gastric acid secretion, and acid secretion in response to a variety of stimuli, including meals, histamine, pentagastrin, and coffee. Activity is apparent 30 minutes after oral administration and persists for at least 3 hours. In general, the effects of 50 mcg were modest and shorter lived, and only the 200-mcg dose had substantial effects on nocturnal secretion or on histamine and meal-stimulated secretion.

Uterine effects

Cytotec has been shown to produce uterine contractions that may endanger pregnancy. (See boxed WARNINGS.)

Other pharmacologic effects

Cytotec does not produce clinically significant effects on serum levels of prolactin, gonadotropins, thyroid-stimulating hormone, growth hormone, thyroxine, cortisol, gastrointestinal hormones (somatostatin, gastrin, vasoactive intestinal polypeptide, and motilin), creatinine, or uric acid. Gastric emptying, immunologic competence, platelet aggregation, pulmonary function, or the cardiovascular system are not modified by recommended doses of Cytotec.

Clinical studies

In a series of small short-term (about 1 week) placebo-controlled studies in healthy human volunteers, doses of misoprostol were evaluated for their ability to reduce the risk of NSAID-induced mucosal injury. Studies of 200 mcg q.i.d. of misoprostol with tolmetin and naproxen, and of 100 and 200 mcg q.i.d. with ibuprofen, all showed reduction of the rate of significant endoscopic injury from about 70–75% on placebo to 10–30% on misoprostol. Doses of 25–200 mcg q.i.d. reduced aspirin-induced mucosal injury and bleeding.

Reducing the risk of gastric ulcers caused by nonsteroidal anti-inflammatory drugs (NSAIDs)

Two 12-week, randomized, double-blind trials in osteoarthritic patients who had gastrointestinal symptoms but no ulcer on endoscopy while taking an NSAID compared the ability of 200 mcg of Cytotec, 100 mcg of Cytotec, and placebo to reduce the risk of gastric ulcer (GU) formation. Patients were approximately equally divided between ibuprofen, piroxicam, and naproxen, and continued this treatment throughout the 12 weeks. The 200-mcg dose caused a marked, statistically significant reduction in gastric ulcers in both studies. The lower dose was somewhat less effective, with a significant result in only one of the studies.

Reduction of Risk of Gastric Ulcers Induced by Ibuprofen, Piroxicam, or Naproxen [No. of patients with ulcer(s) (%)]
 | Therapy Duration
Therapy | 4 weeks | 8 weeks | 12 weeks
Study No. 1
Cytotec 200 mcg q.i.d. (n=74) | 1 (1.4) | 0 | 0 | 1 (1.4) [Statistically significantly different from placebo at the 5% level.]
Cytotec 100 mcg q.i.d. (n=77) | 3 (3.9) | 1 (1.3) | 1 (1.3) | 5 (6.5)
Placebo (n=76) | 11 (14.5) | 4 (5.3) | 4 (5.3) | 19 (25.0)
Study No. 2
Cytotec 200 mcg q.i.d. (n=65) | 1 (1.5) | 1 (1.5) | 0 | 2 (3.1)
Cytotec 100 mcg q.i.d. (n=66) | 2 (3.0) | 2 (3.0) | 1 (1.5) | 5 (7.6)
Placebo (n=62) | 6 (9.7) | 2 (3.2) | 3 (4.8) | 11 (17.7)
Studies No. 1 & No. 2 [Combined data from Study No. 1 and Study No. 2.]
Cytotec 200 mcg q.i.d. (n=139) | 2 (1.4) | 1 (0.7) | 0 | 3 (2.2)
Cytotec 100 mcg q.i.d. (n=143) | 5 (3.5) | 3 (2.1) | 2 (1.4) | 10 (7.0)
Placebo (n=138) | 17 (12.3) | 6 (4.3) | 7 (5.1) | 30 (21.7)

In these trials there were no significant differences between Cytotec and placebo in relief of day or night abdominal pain. No effect of Cytotec in reducing the risk of duodenal ulcers was demonstrated, but relatively few duodenal lesions were seen.

In another clinical trial, 239 patients receiving aspirin 650–1300 mg q.i.d. for rheumatoid arthritis who had endoscopic evidence of duodenal and/or gastric inflammation were randomized to misoprostol 200 mcg q.i.d. or placebo for 8 weeks while continuing to receive aspirin. The study evaluated the possible interference of Cytotec on the efficacy of aspirin in these patients with rheumatoid arthritis by analyzing joint tenderness, joint swelling, physician's clinical assessment, patient's assessment, change in ARA classification, change in handgrip strength, change in duration of morning stiffness, patient's assessment of pain at rest, movement, interference with daily activity, and ESR. Cytotec did not interfere with the efficacy of aspirin in these patients with rheumatoid arthritis.

INDICATIONS AND USAGE

Cytotec (misoprostol) is indicated for reducing the risk of NSAID (nonsteroidal anti-inflammatory drugs, including aspirin)–induced gastric ulcers in patients at high risk of complications from gastric ulcer, e.g., the elderly and patients with concomitant debilitating disease, as well as patients at high risk of developing gastric ulceration, such as patients with a history of ulcer. Cytotec has not been shown to reduce the risk of duodenal ulcers in patients taking NSAIDs. Cytotec should be taken for the duration of NSAID therapy. Cytotec has been shown to reduce the risk of gastric ulcers in controlled studies of 3 months' duration. It had no effect, compared to placebo, on gastrointestinal pain or discomfort associated with NSAID use.

CONTRAINDICATIONS

See boxed WARNINGS.

Cytotec should not be taken by pregnant women to reduce the risk of ulcers induced by nonsteroidal anti-inflammatory drugs (NSAIDs).

Cytotec should not be taken by anyone with a history of allergy to prostaglandins.

WARNINGS

See boxed WARNINGS.

For hospital use only if misoprostol were to be used for cervical ripening, induction of labor, or for the treatment of serious post-partum hemorrhage, which are outside of the approved indication.

PRECAUTIONS

Caution should be employed when administering Cytotec (misoprostol) to patients with pre-existing cardiovascular disease.

Information for patients

Women of childbearing potential using Cytotec to decrease the risk of NSAID-induced ulcers should be told that they must not be pregnant when Cytotec therapy is initiated, and that they must use an effective contraception method while taking Cytotec.

See boxed WARNINGS.

Cytotec is intended for administration along with nonsteroidal anti-inflammatory drugs (NSAIDs), including aspirin, to decrease the chance of developing an NSAID-induced gastric ulcer.

Cytotec should be taken only according to the directions given by a physician.

If the patient has questions about or problems with Cytotec, the physician should be contacted promptly.

THE PATIENT SHOULD NOT GIVE CYTOTEC TO ANYONE ELSE. Cytotec has been prescribed for the patient's specific condition, may not be the correct treatment for another person, and may be dangerous to the other person if she were to become pregnant.

The Cytotec package the patient receives from the pharmacist will include a leaflet containing patient information. The patient should read the leaflet before taking Cytotec and each time the prescription is renewed because the leaflet may have been revised.

Keep Cytotec out of the reach of children.

SPECIAL NOTE FOR WOMEN: Cytotec may cause birth defects, abortion (sometimes incomplete), premature labor or rupture of the uterus if given to pregnant women.

Cytotec is available only as a unit-of-use package that includes a leaflet containing patient information. See Patient Information at the end of this labeling.

Drug interactions

See Clinical Pharmacology. Cytotec has not been shown to interfere with the beneficial effects of aspirin on signs and symptoms of rheumatoid arthritis. Cytotec does not exert clinically significant effects on the absorption, blood levels, and antiplatelet effects of therapeutic doses of aspirin. Cytotec has no clinically significant effect on the kinetics of diclofenac or ibuprofen.

Prostaglandins such as Cytotec may augment the activity of oxytocic agents, especially when given less than 4 hours prior to initiating oxytocin treatment. Concomitant use is not recommended.

Animal toxicology

A reversible increase in the number of normal surface gastric epithelial cells occurred in the dog, rat, and mouse. No such increase has been observed in humans administered Cytotec for up to 1 year.

An apparent response of the female mouse to Cytotec in long-term studies at 100 to 1000 times the human dose was hyperostosis, mainly of the medulla of sternebrae. Hyperostosis did not occur in long-term studies in the dog and rat and has not been seen in humans treated with Cytotec.

Carcinogenesis, mutagenesis, impairment of fertility

There was no evidence of an effect of Cytotec on tumor occurrence or incidence in rats receiving daily doses up to 150 times the human dose for 24 months. Similarly, there was no effect of Cytotec on tumor occurrence or incidence in mice receiving daily doses up to 1000 times the human dose for 21 months. The mutagenic potential of Cytotec was tested in several in vitro assays, all of which were negative.

Misoprostol, when administered to breeding male and female rats at doses 6.25 times to 625 times the maximum recommended human therapeutic dose, produced dose-related pre- and post-implantation losses and a significant decrease in the number of live pups born at the highest dose. These findings suggest the possibility of a general adverse effect on fertility in males and females.

Pregnancy

Teratogenic effects

See boxed WARNINGS. Congenital anomalies sometimes associated with fetal death have been reported subsequent to the unsuccessful use of misoprostol as an abortifacient, but the drug's teratogenic mechanism has not been demonstrated. Several reports in the literature associate the use of misoprostol during the first trimester of pregnancy with skull defects, cranial nerve palsies, facial malformations, and limb defects.

Cytotec is not fetotoxic or teratogenic in rats and rabbits at doses 625 and 63 times the human dose, respectively.

Nonteratogenic effects

See boxed WARNINGS. Cytotec may endanger pregnancy (may cause abortion) and thereby cause harm to the fetus when administered to a pregnant woman. Cytotec may produce uterine contractions, uterine bleeding, and expulsion of the products of conception. Abortions caused by Cytotec may be incomplete. If a woman is or becomes pregnant while taking this drug to reduce the risk of NSAID-induced ulcers, the drug should be discontinued and the patient apprised of the potential hazard to the fetus.

Labor and delivery

Cytotec can induce or augment uterine contractions. Vaginal administration of Cytotec, outside of its approved indication, has been used as a cervical ripening agent, for the induction of labor and for treatment of serious postpartum hemorrhage in the presence of uterine atony. A major adverse effect of the obstetrical use of Cytotec is uterine tachysystole which may progress to uterine tetany with marked impairment of uteroplacental blood flow, uterine rupture (requiring surgical repair, hysterectomy, and/or salpingo-oophorectomy), or amniotic fluid embolism and lead to adverse fetal heart changes. Uterine activity and fetal status should be monitored by trained obstetrical personnel in a hospital setting.

The risk of uterine rupture associated with misoprostol use in pregnancy increases with advancing gestational ages and prior uterine surgery, including Cesarean delivery. Grand multiparity also appears to be a risk factor for uterine rupture.

The use of Cytotec outside of its approved indication may also be associated with meconium passage, meconium staining of amniotic fluid, and Cesarean delivery. Maternal shock, maternal death, fetal bradycardia, and fetal death have also been reported with the use of misoprostol.

Cytotec should not be used in the third trimester in women with a history of Cesarean section or major uterine surgery because of an increased risk of uterine rupture. Cytotec should not be used in cases where uterotonic drugs are generally contraindicated or where hyperstimulation of the uterus is considered inappropriate, such as cephalopelvic disproportion, grand multiparity, hypertonic or hyperactive uterine patterns, or fetal distress where delivery is not imminent, or when surgical intervention is more appropriate.

The effect of Cytotec on later growth, development, and functional maturation of the child when Cytotec is used for cervical ripening or induction of labor has not been established. Information on Cytotec's effect on the need for forceps delivery or other intervention is unknown.

The use of Cytotec (misoprostol) for the management of postpartum hemorrhage has been associated with reports of high fevers (greater than 40 degrees Celsius or 104 degrees Fahrenheit), accompanied by autonomic and central nervous system effects, such as tachycardia, disorientation, agitation, and convulsions. These fevers were transient in nature. Supportive therapy should be dictated by the patient's clinical presentation.

Nursing mothers

Misoprostol is rapidly metabolized in the mother to misoprostol acid, which is biologically active and is excreted in breast milk. There are no published reports of adverse effects of misoprostol in breast-feeding infants of mothers taking misoprostol. Caution should be exercised when misoprostol is administered to a nursing woman.

Pediatric use

Safety and effectiveness of Cytotec in pediatric patients have not been established.

ADVERSE REACTIONS

The following have been reported as adverse events in subjects receiving Cytotec:

Gastrointestinal

In subjects receiving Cytotec 400 or 800 mcg daily in clinical trials, the most frequent gastrointestinal adverse events were diarrhea and abdominal pain. The incidence of diarrhea at 800 mcg in controlled trials in patients on NSAIDs ranged from 14–40% and in all studies (over 5,000 patients) averaged 13%. Abdominal pain occurred in 13–20% of patients in NSAID trials and about 7% in all studies, but there was no consistent difference from placebo.

Diarrhea was dose related and usually developed early in the course of therapy (after 13 days), usually was self-limiting (often resolving after 8 days), but sometimes required discontinuation of Cytotec (2% of the patients). Rare instances of profound diarrhea leading to severe dehydration have been reported. Patients with an underlying condition such as inflammatory bowel disease, or those in whom dehydration, were it to occur, would be dangerous, should be monitored carefully if Cytotec is prescribed. The incidence of diarrhea can be minimized by administering after meals and at bedtime, and by avoiding coadministration of Cytotec with magnesium-containing antacids.

Gynecological

Women who received Cytotec during clinical trials reported the following gynecological disorders: spotting (0.7%), cramps (0.6%), hypermenorrhea (0.5%), menstrual disorder (0.3%) and dysmenorrhea (0.1%). Postmenopausal vaginal bleeding may be related to Cytotec administration. If it occurs, diagnostic workup should be undertaken to rule out gynecological pathology. (See boxed WARNINGS.)

Elderly

There were no significant differences in the safety profile of Cytotec in approximately 500 ulcer patients who were 65 years of age or older compared with younger patients.

Additional adverse events which were reported are categorized as follows:

Incidence greater than 1%

In clinical trials, the following adverse reactions were reported by more than 1% of the subjects receiving Cytotec and may be causally related to the drug: nausea (3.2%), flatulence (2.9%), headache (2.4%), dyspepsia (2.0%), vomiting (1.3%), and constipation (1.1%). However, there were no significant differences between the incidences of these events for Cytotec and placebo.

Causal relationship unknown

The following adverse events were infrequently reported. Causal relationships between Cytotec and these events have not been established but cannot be excluded:

Body as a whole: aches/pains, asthenia, fatigue, fever, chills, rigors, weight changes.

Skin: rash, dermatitis, alopecia, pallor, breast pain.

Special senses: abnormal taste, abnormal vision, conjunctivitis, deafness, tinnitus, earache.

Respiratory: upper respiratory tract infection, bronchitis, bronchospasm, dyspnea, pneumonia, epistaxis.

Cardiovascular: chest pain, edema, diaphoresis, hypotension, hypertension, arrhythmia, phlebitis, increased cardiac enzymes, syncope, myocardial infarction (some fatal), thromboembolic events (e.g., pulmonary embolism, arterial thrombosis, and CVA).

Gastrointestinal: GI bleeding, GI inflammation/infection, rectal disorder, abnormal hepatobiliary function, gingivitis, reflux, dysphagia, amylase increase.

Hypersensitivity: anaphylactic reaction

Metabolic: glycosuria, gout, increased nitrogen, increased alkaline phosphatase.

Genitourinary: polyuria, dysuria, hematuria, urinary tract infection.

Nervous system/Psychiatric: anxiety, change in appetite, depression, drowsiness, dizziness, thirst, impotence, loss of libido, sweating increase, neuropathy, neurosis, confusion.

Musculoskeletal: arthralgia, myalgia, muscle cramps, stiffness, back pain.

Blood/Coagulation: anemia, abnormal differential, thrombocytopenia, purpura, ESR increased.

OVERDOSAGE

The toxic dose of Cytotec in humans has not been determined. Cumulative total daily doses of 1600 mcg have been tolerated, with only symptoms of gastrointestinal discomfort being reported. In animals, the acute toxic effects are diarrhea, gastrointestinal lesions, focal cardiac necrosis, hepatic necrosis, renal tubular necrosis, testicular atrophy, respiratory difficulties, and depression of the central nervous system. Clinical signs that may indicate an overdose are sedation, tremor, convulsions, dyspnea, abdominal pain, diarrhea, fever, palpitations, hypotension, or bradycardia. Symptoms should be treated with supportive therapy.

It is not known if misoprostol acid is dialyzable. However, because misoprostol is metabolized like a fatty acid, it is unlikely that dialysis would be appropriate treatment for overdosage.

DOSAGE AND ADMINISTRATION

The recommended adult oral dose of Cytotec for reducing the risk of NSAID-induced gastric ulcers is 200 mcg four times daily with food. If this dose cannot be tolerated, a dose of 100 mcg can be used. (See Clinical Pharmacology: Clinical studies.) Cytotec should be taken for the duration of NSAID therapy as prescribed by the physician. Cytotec should be taken with a meal, and the last dose of the day should be at bedtime.

Renal impairment

Adjustment of the dosing schedule in renally impaired patients is not routinely needed, but dosage can be reduced if the 200-mcg dose is not tolerated. (See Clinical Pharmacology.)

HOW SUPPLIED

Cytotec 100-mcg tablets are white, round, with SEARLE debossed on one side and 1451 on the other side; supplied as:

NDC Number | Size
0025-1451-60 | unit-of-use bottle of 60
0025-1451-34 | carton of 100 unit dose

Cytotec 200-mcg tablets are white, hexagonal, with SEARLE debossed above and 1461 debossed below the line on one side and a double stomach debossed on the other side; supplied as:

NDC Number | Size
0025-1461-60 | unit-of-use bottle of 60
0025-1461-31 | unit-of-use bottle of 100
0025-1461-34 | carton of 100 unit dose

STORAGE AND HANDLING

Store at or below 25°C (77°F), in a dry area.

This product's labeling may have been updated. For the most recent prescribing information, please visit www.pfizer.com.

LAB-0170-9.0
Revised February 2025

PATIENT INFORMATION

Read this leaflet before taking Cytotec® (misoprostol) and each time your prescription is renewed, because the leaflet may be changed.

Cytotec (misoprostol) is being prescribed by your doctor to decrease the chance of getting stomach ulcers related to the arthritis/pain medication that you take.

Do not take Cytotec to reduce the risk of NSAID-induced ulcers if you are pregnant. (See boxed WARNINGS.) Cytotec can cause abortion (sometimes incomplete which could lead to dangerous bleeding and require hospitalization and surgery), premature birth, or birth defects. It is also important to avoid pregnancy while taking this medication and for at least one month or through one menstrual cycle after you stop taking it. Cytotec may cause the uterus to tear (uterine rupture) during pregnancy. The risk of uterine rupture increases as your pregnancy advances and if you have had surgery on the uterus, such as a Cesarean delivery. Rupture (tearing) of the uterus can result in severe bleeding, hysterectomy, and/or maternal or fetal death.

If you become pregnant during Cytotec therapy, stop taking Cytotec and contact your physician immediately. Remember that even if you are on a means of birth control it is still possible to become pregnant. Should this occur, stop taking Cytotec and contact your physician immediately.

Cytotec may cause diarrhea, abdominal cramping, and/or nausea in some people. In most cases these problems develop during the first few weeks of therapy and stop after about a week. You can minimize possible diarrhea by making sure you take Cytotec with food.

Because these side effects are usually mild to moderate and usually go away in a matter of days, most patients can continue to take Cytotec. If you have prolonged difficulty (more than 8 days), or if you have severe diarrhea, cramping and/or nausea, call your doctor.

Take Cytotec only according to the directions given by your physician.

Do not give Cytotec to anyone else. It has been prescribed for your specific condition, may not be the correct treatment for another person, and would be dangerous if the other person were pregnant.

This information sheet does not cover all possible side effects of Cytotec. This patient information leaflet does not address the side effects of your arthritis/pain medication. See your doctor if you have questions.

Keep out of reach of children.

This product's labeling may have been updated. For the most recent prescribing information, please visit www.pfizer.com.

LAB-0172-5.0
Revised February 2025

PRINCIPAL DISPLAY PANEL - 100 mcg Tablet Blister Pack

NDC 0025-1451-34

Cytotec®
misoprostol tablets
100 mcg

Distributed by Pfizer Labs
Division of Pfizer Inc., NY, NY 10001

EXP. YYYY.MM.DD
LOT A01234

21542269

PRINCIPAL DISPLAY PANEL - 100 mcg Tablet Blister Pack Carton

Pfizer

Cytotec® 100 mcg
misoprostol tablets

100 Tablets
For in-institution use only

PRINCIPAL DISPLAY PANEL - 100 mcg Tablet Bottle Label

Pfizer

NDC 0025-1451-60

Cytotec®
misoprostol tablets
100 mcg
60 Tablets

Distributed by
Pfizer Labs
Division of Pfizer Inc,
New York, NY 10001

Rx only

PRINCIPAL DISPLAY PANEL - 200 mcg Tablet Blister Pack

NDC 0025-1461-34

Cytotec®
misoprostol tablets
200 mcg

Distributed by G.D. Searle LLC
Division of Pfizer Inc. NY, NY 10017

EXP: YYYY.MM.DD
LOT A01234

21540995

PRINCIPAL DISPLAY PANEL - 200 mcg Tablet Blister Pack Carton

Pfizer

Cytotec® 200 mcg
misoprostol tablets

100 Tablets
For in-institution use only

PRINCIPAL DISPLAY PANEL - 200 mcg Tablet Bottle Label

Pfizer

NDC 0025-1461-60

Cytotec®
misoprostol tablets
200 mcg
60 Tablets

Distributed by
Pfizer Labs
Division of Pfizer Inc,
New York, NY 10001

Rx only